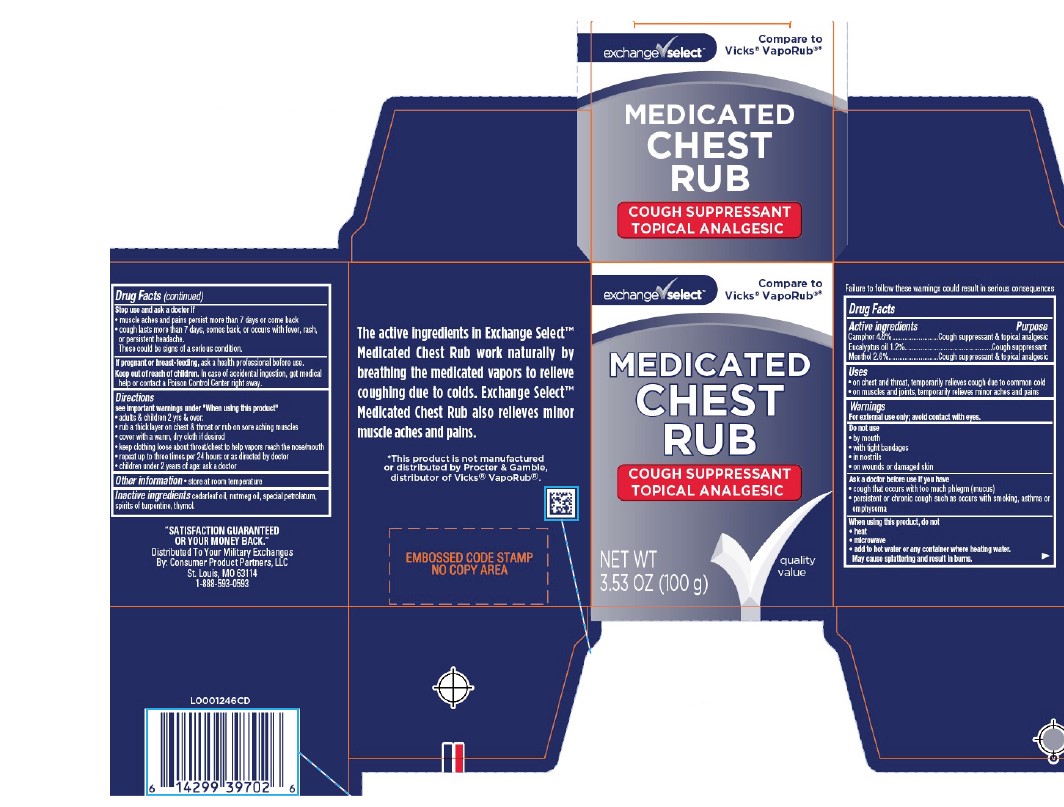 DRUG LABEL: Chest Rub
NDC: 55301-248 | Form: JELLY
Manufacturer: Your Military Exchanges
Category: otc | Type: HUMAN OTC DRUG LABEL
Date: 20260212

ACTIVE INGREDIENTS: EUCALYPTUS OIL 12 mg/1 g; MENTHOL 26 mg/1 g; CAMPHOR (SYNTHETIC) 48 mg/1 g
INACTIVE INGREDIENTS: TURPENTINE OIL; THYMOL; CEDAR LEAF OIL; NUTMEG OIL; PETROLATUM

Exchange Select 248.001/248AI
Medicated Chest Rub

Warning

Failure to follow these warning could result in serious consequences

Active ingredients

Camphor 4.8%

Eucalyptus oil 1.2%

Menthol 2.6%

Purpose

Cough Suppressant & topical analgesic

Uses

- on chest & throat, temporarily relieves cough due to the common cold
- on muscles and joints, temporarily relieves minor aches and pains

Warnings

For external use only; avoid contact with eyes.

Do not use

- by mouth
- with tight bandages
- in nostrils
- on wounds or damaged skin

Ask a doctor before use if you have

- cough that occurs with too much phlegm (mucus)
- persistent or chronic cough such as occurs with smoking, asthma or emphysema

When using this product, do not

- heat
- microwave
- add to hot water or any container where heating water. May cause splattering and result in burns.

Stop use and ask a doctor if

- muscle aches and pains persist more than 7 days or come back
- cough lasts more than 7 days, comes back, or occurs with fever, rash, or persistent headache

These could be signs of a serious condition.

If pregnant or breast-feeding,

ask a health professional before use.

Keep out of reach of children.

In case of accidental ingestion, get medical help or contact a Poison Control Center right away.

Directions

see important warnings under “When using this product”

- adults & children 2 yrs & over:
- rub a thick layer on chest & throat or rub on sore aching muscles
- cover with a warm, dry cloth if desired
- keep clothing loose about throat/chest to help vapors reach the nose/mouth
- repeat up to three times per 24 hours or as directed by doctor
- children under 2 years of age: ask a doctor

Other information

- store at room temperature

Inactive ingredients

cedarleaf oil, nutmeg oil, special petrolatum, spirits of turpentine, thymol

Disclamier

The active ingredients in Exchange Select™ Medicated Chest Rub work naturally by breathing the medicated vapors to relieve coughing due to colds. Echange Select™ Medicated Chest Rub also relieves minor muscle aches and pains.

*This product is not manufactured or distributed by Procter & Gamble, distributor of Vicks®VapoRub.

Adverse Reaction

"SATISFACTION GUARANTEED OR YOUR MONEY BACK."

Distributed To Your Military Exchanges

By: Consumer Product Partners, LLC

St. Louis, MO 63114

1-888-593-0593

Principal Panel Display

exchange select™

Compare to Vicks®VapoRub®*

MEDICATED CHEST RUB

COUGH SUPPRESSANT

TOPICAL ANALGESIC

NET WT 3.53 OZ (100 g)

quality value